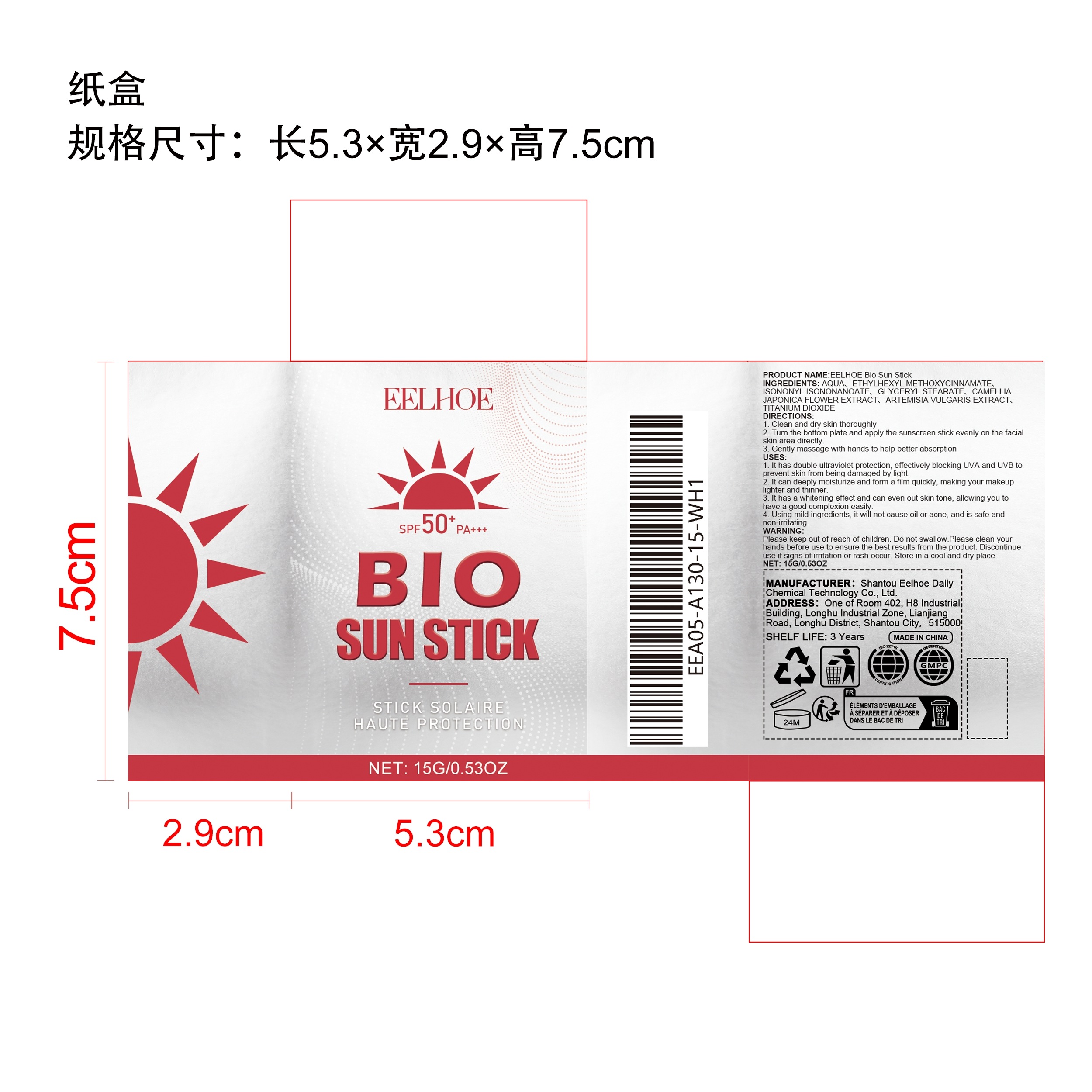 DRUG LABEL: EELHOE Bio Sun Stick
NDC: 85064-008 | Form: STICK
Manufacturer: Shantou Eelhoe Daily Chemical Technology Co., Ltd.
Category: otc | Type: HUMAN OTC DRUG LABEL
Date: 20251127

ACTIVE INGREDIENTS: CAMELLIA JAPONICA FLOWER 0.03 mg/15 mg; ARTEMISIA VULGARIS ROOT 0.03 mg/15 mg
INACTIVE INGREDIENTS: ISONONYL ISONONANOATE 0.6 mg/15 mg; TITANIUM DIOXIDE 0.03 mg/15 mg; AQUA 13.335 mg/15 mg; GLYCERYL STEARATE 0.225 mg/15 mg; ETHYLHEXYL METHOXYCINNAMATE 0.75 mg/15 mg

ACTIVE INGREDIENT

CAMELLIA JAPONICA FLOWER EXTRACT、
ARTEMISIA VULGARIS EXTRACT

PURPOSE

1. It has double ultraviolet protection, effectively blocking UVA and UVB to prevent skin from being damaged by light.

2. It can deeply moisturize and form a film quickly, making your makeup lighter and thinner.

3. It has a whitening effect and can even out skin tone, allowing you to have a good complexion easily.

4. Using mild ingredients, it will not cause oil or acne, and is safe and non-irritating.

STOP USE

1. Clean and dry skin thoroughly

2. Turn the bottom plate and apply the sunscreen stick evenly on the facial skin area directly.

3. Gently massage with hands to help better absorption

WARNINGS

Please keep out of reach of children. Do not swallow.Please clean your hands before use to ensure the best results from the product. Discontinue use if signs of irritation or rash occur. Store in a cool and dry place.

DO NOT USE

Discontinue use if signs of irritation or rash occur.

STOP USE

Discontinue use if signs of irritation or rash occur.

KEEP OUT OF REACH OF CHILDREN

Please keep out of reach of children. Do not swallow.

STORAGE AND HANDLING

Store in a cool and dry place.

INACTIVE INGREDIENT

AQUA、
ETHYLHEXYL METHOXYCINNAMATE、
ISONONYL ISONONANOATE、
GLYCERYL STEARATE、

TITANIUM DIOXIDE